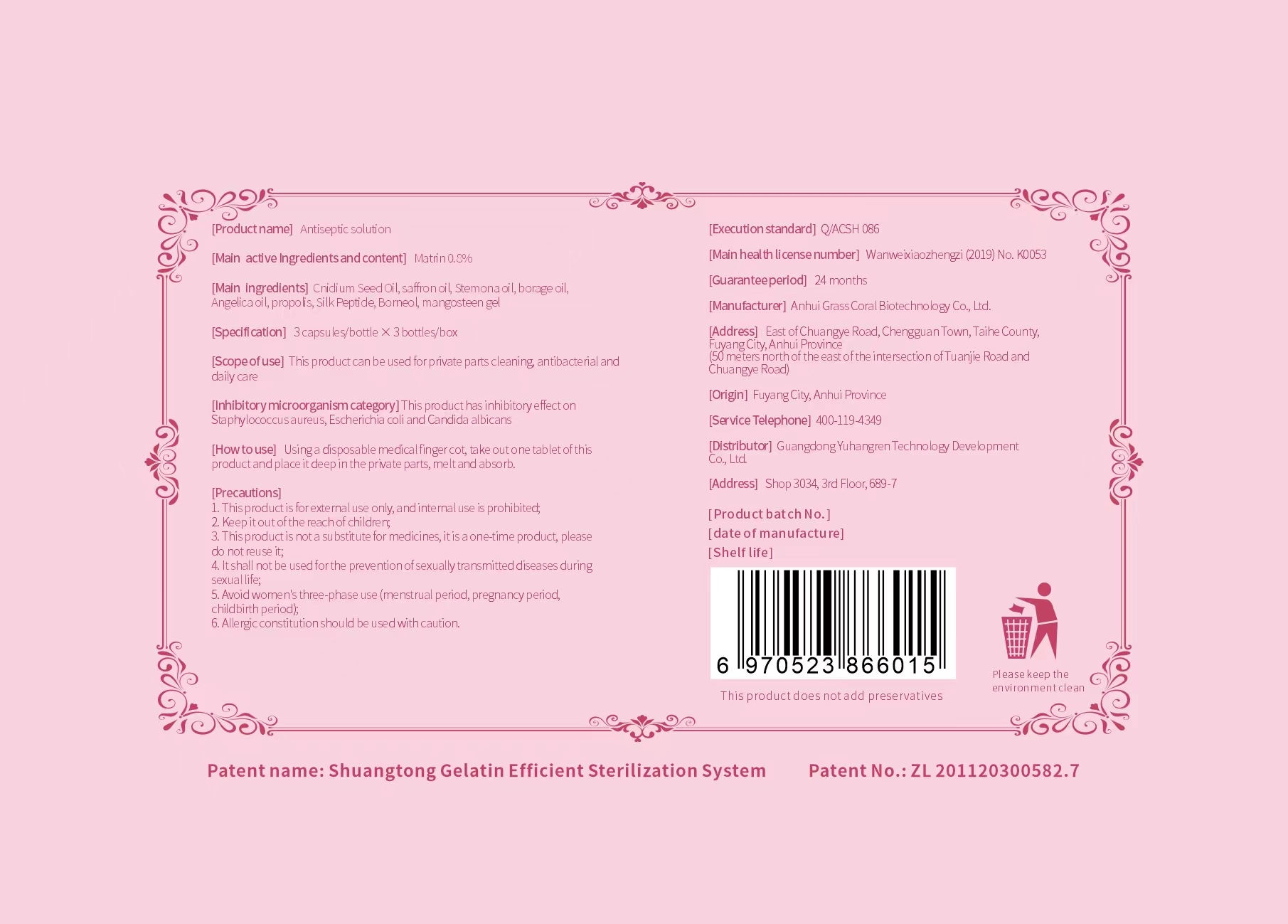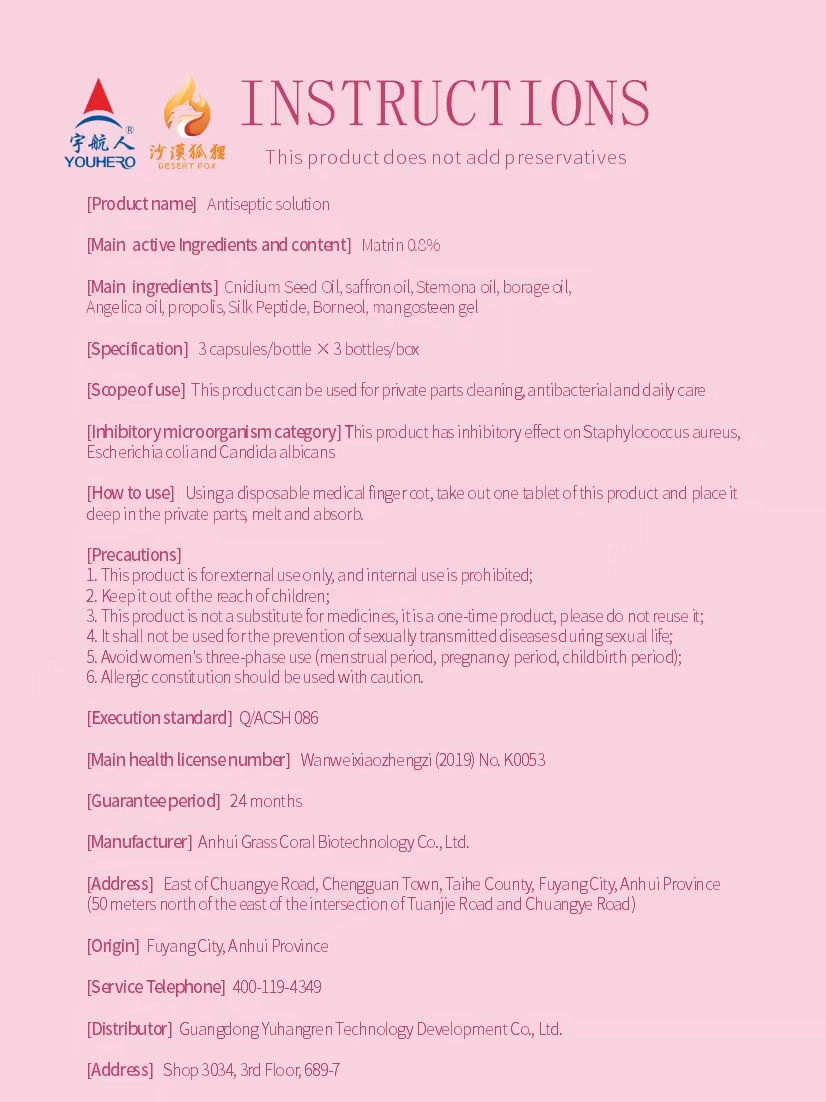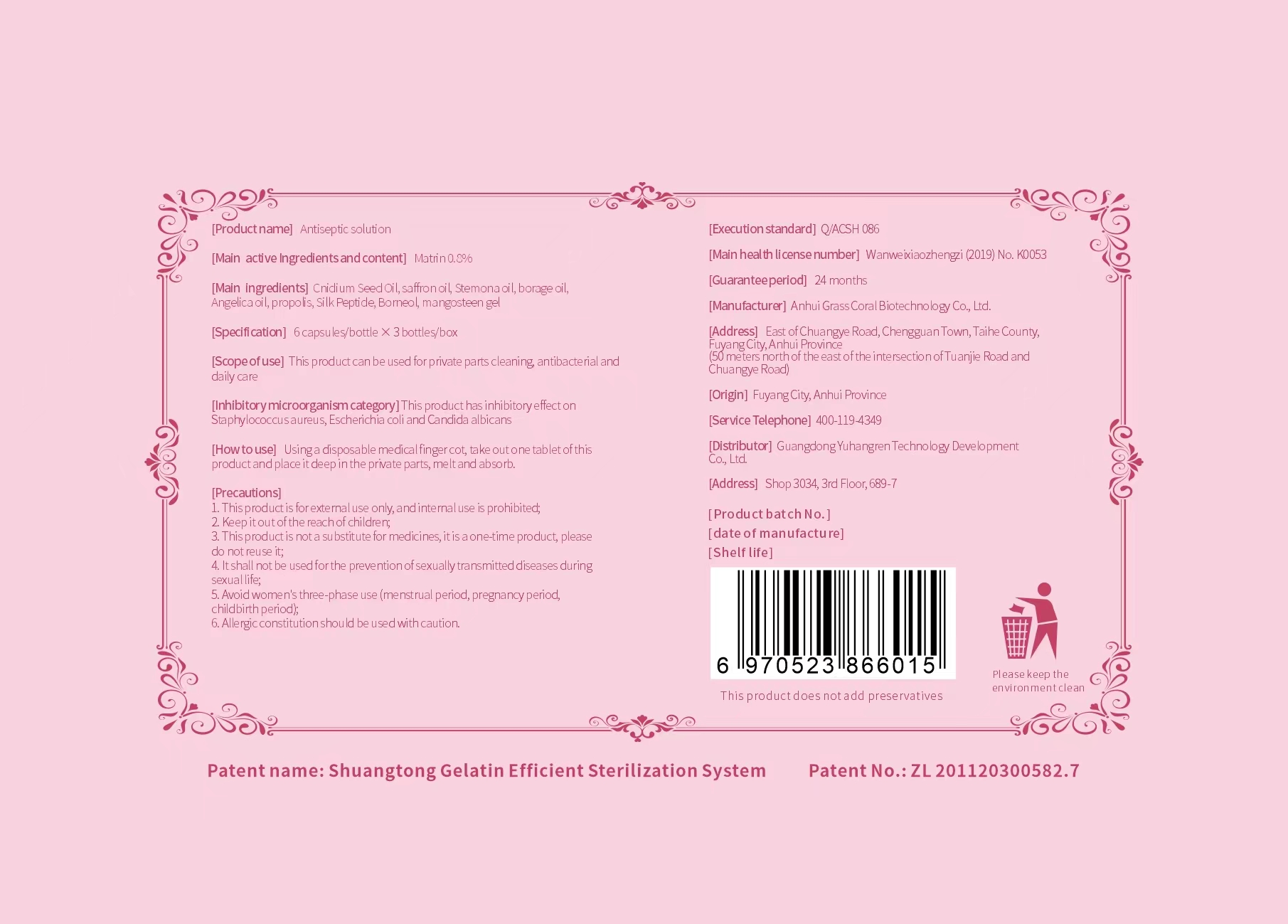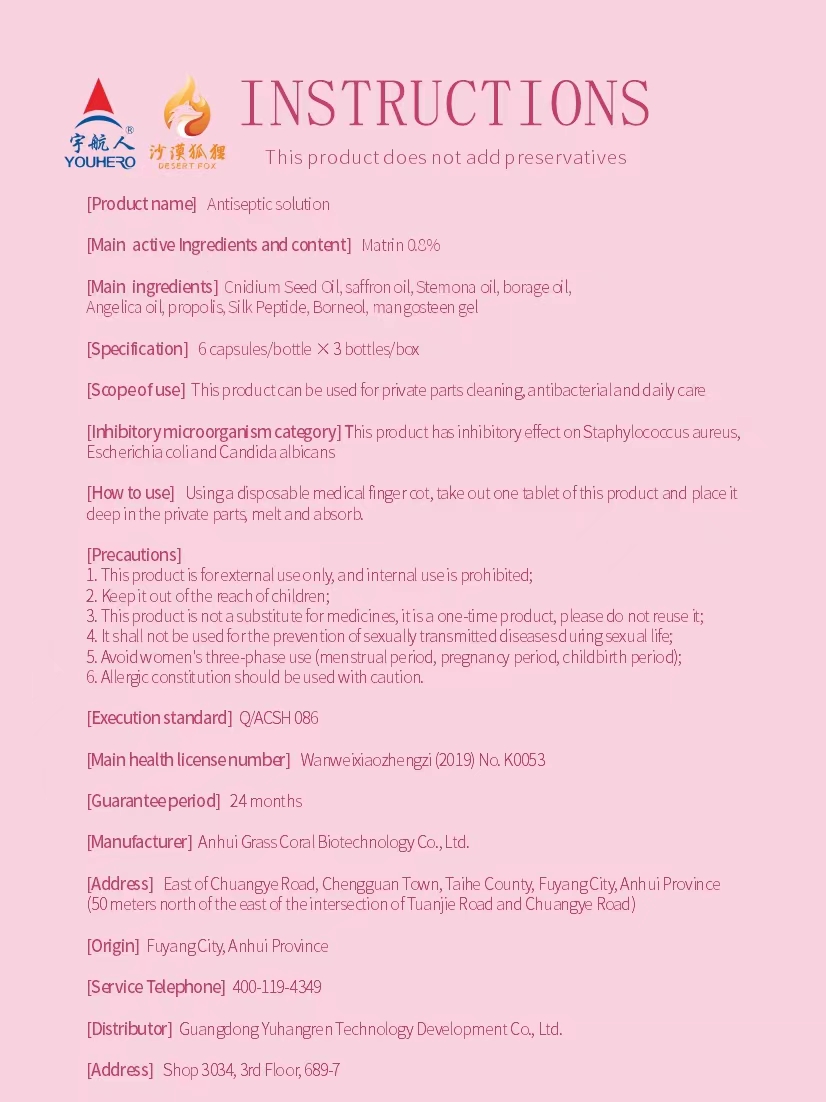 DRUG LABEL: antiseptic solution
NDC: 83091-001 | Form: CAPSULE
Manufacturer: Anhui Cao coral biology science and technology co., ltd
Category: otc | Type: HUMAN OTC DRUG LABEL
Date: 20221107

ACTIVE INGREDIENTS: MATRINE 0.8 g/100 1
INACTIVE INGREDIENTS: LIGHT NAPHTHA; OSTHOL; ANGELICA SEED OIL; CNIDIUM MONNIERI FRUIT; DOCUSATE SODIUM; BORNEOL; PROPOLIS WAX; MANGOSTIN; PAREPTIDE

83091-001
antiseptic solution

active ingredients

Matrine 0.8%(m/M0)

Usage

This product can be used for private body part cleaning, bacteriostasis and daily care.

Directions

Using disposable medical finger cots,take out one capsule of this product and place it deep into the virginia for melting and absorbing.

Other information

1.This product is for external use only.

2.Keep out of reach of children.

3.This product is not a substitute for other medication.

4 should not be used for the prevention of sexually transmitted diseases.

5.Avoid use during menstrual period, pregnancy, giving birth.

6,stop use if allergic.

Inactive Ingredients

Cnidium Seed Oil
saffron oil
Stemona oil
borage oil
Angelica oil
propolis
Silk Peptide
Borneol
mangosteen gel

Package Label - Principal Display Panel

OUTERMOST LEVEL
83091-001-01
3 Bottle in 1 Box
INNERMOST LEVEL
83091-001-11
3 Capsules in 1 Bottle

OUTERMOST LEVEL
83091-001-02
3 Bottle in 1 Box
INNERMOST LEVEL
83091-001-12
3 Capsules in 1 Bottle

OUTERMOST LEVEL
83091-001-03
3 Bottle in 1 Box
INNERMOST LEVEL
83091-001-13
6 Capsules in 1 Bottle

OUTERMOST LEVEL
83091-001-04
3 Bottle in 1 Box
INNERMOST LEVEL
83091-001-14
6 Capsules in 1 Bottle